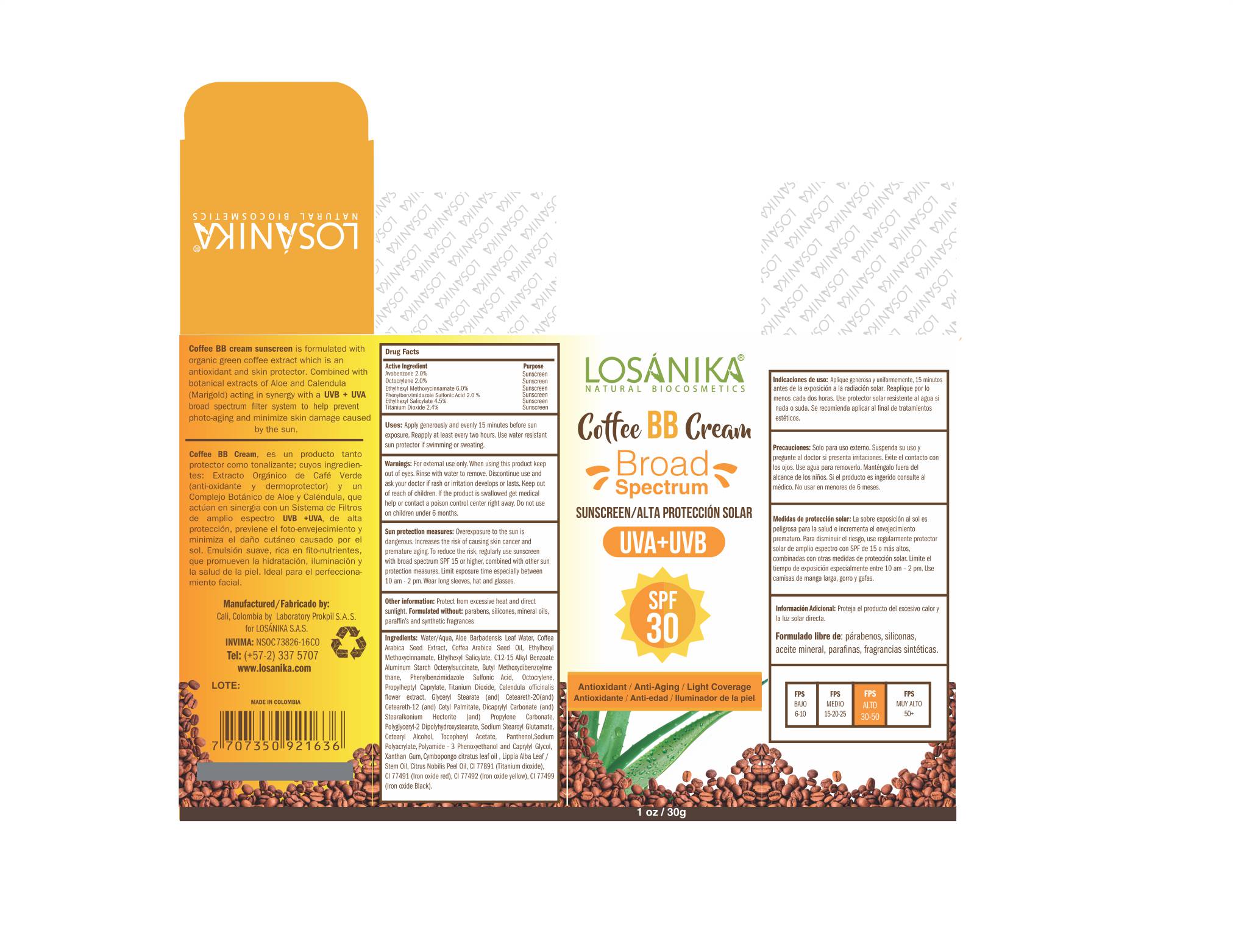 DRUG LABEL: OCTINOXATE,OCTISALATE,AVOBENZONE,OCTOCRYLENE,ENSULIZOLE,TITANIUM DIOXIDE
NDC: 71801-541 | Form: CREAM
Manufacturer: PROKPIL SAS
Category: otc | Type: HUMAN OTC DRUG LABEL
Date: 20210202

ACTIVE INGREDIENTS: OCTISALATE 4.5 g/100 g; OCTOCRYLENE 2 g/100 g; ENSULIZOLE 2 g/100 g; AVOBENZONE 2 g/100 g; OCTINOXATE 6 g/100 g; TITANIUM DIOXIDE 2.4 g/100 g
INACTIVE INGREDIENTS: CALENDULA OFFICINALIS FLOWER; FERRIC OXIDE RED; SODIUM STEAROYL GLUTAMATE; GLYCERIN; POLYAMIDE-3 (12000 MW); PROPYLENE CARBONATE; CAPRYLYL GLYCOL; FERROSOFERRIC OXIDE; WEST INDIAN LEMONGRASS OIL; LIPPIA ALBA WHOLE; MANDARIN OIL; FERRIC OXIDE YELLOW; SODIUM ACRYLATE; .ALPHA.-TOCOPHEROL ACETATE; WATER; ARABICA COFFEE BEAN; ARABICA COFFEE OIL; ALUMINUM STARCH OCTENYLSUCCINATE; PROPYLHEPTYL CAPRYLATE; DICAPRYLYL CARBONATE; PANTHENOL; POLYGLYCERYL-2 DIPOLYHYDROXYSTEARATE; ALKYL (C12-15) BENZOATE; STEARALKONIUM HECTORITE; CETOSTEARYL ALCOHOL; PHENOXYETHANOL; ALOE VERA LEAF; XANTHAN GUM

LOSANIKA COFFEE BB CREAM BROAD SPECTRUM SPF 30 - Avobenzone 2%,Octocrylene 2%,Octinoxate 6%,Ensulizole 2%,Octisalate 4.5%. Titanium Dioxide 2.4% CREAM

Disclaimer: Most OTC drugs are not reviewed and approved by FDA, however they may be marketed if they comply with applicable regulations and policies. FDA has not evaluated whether this product complies.

PURPOSE:

Sunscreen

Active Ingredients:

AVOBENZONE 2%

OCTOCRYLENE 2%

OCTINOXATE 6%

ENSULIZOLE 2%

OCTISALATE 4.5%

TITANIUM DIOXIDE 2.4%

USES:

For all sunscreen drug products:
“helps prevent sunburn

WARNING:

For external use only

When using this product:

keep out of eyes. Rinse with water to remove.

Stop use and ask a Doctor:

if rash or irritation develops or lasts.

Keep out of reach of children:

If the product is swallowed get medical help or contact a poison control center right away.

Directions:

Apply generously and evenly 15 minutes before sun exposure

Reapply at least every two hours
Use water resistant sun protector if swimming or sweating.
Sun protection measures:
Overexposure to the sun is dangerous. Increases the risk of causing skin cancer and premature aging.
To reduce the risk, regularly use sunscreen with broad spectrum SPF 15 or higher, combined with other sun protection measures.
Limit exposure time especially between 10 am - 2 pm.
Wear long sleeves, hat and glasses.
Children under 6 months of age ask a doctor.

Inactive Ingredients:

Water/Aqua, Aloe Barbadensis Leaf Water, Coffea Arabica Seed Extract, Coffea Arabica Seed Oil, Ethylhexyl Methoxycinnamate, Ethylhexyl Salicylate, C12-15 Alkyl Benzoate, Aluminum Starch Octenylsuccinate, Butyl Methoxydibenzoylmethane, Phenylbenzimidazole Sulfonic Acid, Octocrylene, Propylheptyl Caprylate,Titanium Dioxide, Calendula officinalis flower extract, Cetearyl Alcohol, Dicaprylyl Carbonate(and)Stearalkonium Hectorite (and) Propylene Carbonate, Polyglyceryl-2 Dipolyhydroxystearate, Sodium Stearoyl Glutamate, Tocopheryl Acetate, Panthenol,Sodium Polyacrylate, Phenoxyethanol and Caprylyl Glycol, Xanthan Gum, Polyamide – 3, Cymbopongo citratus leaf oil , Lippia Alba Leaf/Stem Oil, Citrus nobilis (mandarin orange) peel oil, CI 77891 (Titanium dioxide), CI 77491 (Iron oxide red), CI 77492 (Iron oxide yellow), CI 77499 (Iron oxide Black).

Ohter Information:

Protect from excessive heat and direct sunlight.

Formulated with out:

Parabens, silicones, mineral oils, paraffins and synthetic fragrances